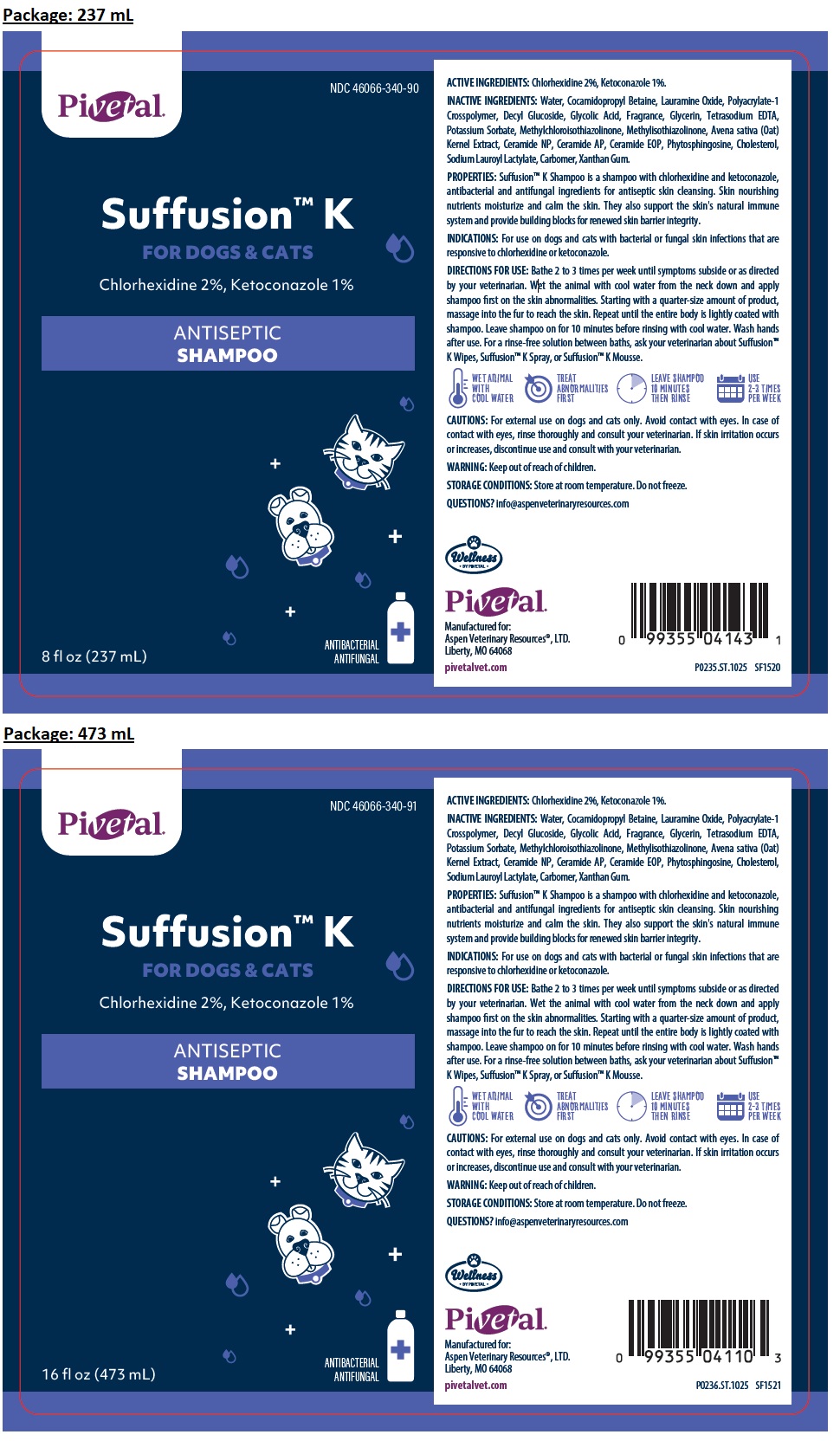 DRUG LABEL: Suffusion K ANTISEPTIC
NDC: 46066-340 | Form: SHAMPOO
Manufacturer: Aspen Veterinary Resources, LTD.
Category: animal | Type: OTC ANIMAL DRUG LABEL
Date: 20251031

ACTIVE INGREDIENTS: CHLORHEXIDINE GLUCONATE 2 g/100 mL; KETOCONAZOLE 1 g/100 mL
INACTIVE INGREDIENTS: WATER; COCAMIDOPROPYL BETAINE; LAURAMINE OXIDE; POLYACRYLATE-1 CROSSPOLYMER; DECYL GLUCOSIDE; GLYCOLIC ACID; GLYCERIN; EDETATE SODIUM; POTASSIUM SORBATE; METHYLCHLOROISOTHIAZOLINONE; METHYLISOTHIAZOLINONE; OAT; CERAMIDE NP; CERAMIDE AP; CERAMIDE 9; PHYTOSPHINGOSINE; CHOLESTEROL; SODIUM LAUROYL LACTYLATE; CARBOMER HOMOPOLYMER, UNSPECIFIED TYPE; XANTHAN GUM

Pivetal® Suffusion™ K ANTISEPTIC SHAMPOO

ACTIVE INGREDIENTS:

Chlorhexidine 2%, Ketoconazole 1%.

INACTIVE INGREDIENTS:

Water, Cocamidopropyl Betaine, Lauramine Oxide, Polyacrylate-1 Crosspolymer, Decyl Glucoside, Glycolic Acid, Fragrance, Glycerin, Tetrasodium EDTA, Potassium Sorbate, Methylchloroisothiazolinone, Methylisothiazolinone, Avena sativa (Oat) Kernel Extract, Ceramide NP, Ceramide AP, Ceramide EOP, Phytosphingosine, Cholesterol, Sodium Lauroyl Lactylate, Carbomer, Xanthan Gum.

PROPERTIES:

Suffusion™ K Shampoo is a shampoo with chlorhexidine and ketoconazole, antibacterial and antifungal ingredients for antiseptic skin cleansing. Skin nourishing nutrients moisturize and calm the skin. They also support the skin's natural immune system and provide building blocks for renewed skin barrier integrity.

INDICATIONS:

For use on dogs and cats with bacterial or fungal skin infections that are responsive to chlorhexidine or ketoconazole.

DIRECTIONS FOR USE:

Bathe 2 to 3 times per week until symptoms subside or as directed by your veterinarian. Wet the animal with cool water from the neck down and apply shampoo first on the skin abnormalities. Starting with a quarter-size amount of product, massage into the fur to reach the skin. Repeat until the entire body is lightly coated with shampoo. Leave shampoo on for 10 minutes before rinsing with cool water. Wash hands after use. For a rinse-free solution between baths, ask your veterinarian about Suffusion™ K Wipes, Suffusion™ K Spray, or Suffusion™ K Mousse.
WET ANIMAL WITH COOL WATER
TREAT ABNORMALITIES FIRST
LEAVE SHAMPOO 10 MINUTES THEN RINSE
USE 2-3 TIMES PER WEEK

CAUTIONS:

For external use on dogs and cats only. Avoid contact with eyes. In case of contact with eyes, rinse thoroughly and consult your veterinarian. If skin irritation occurs or increases, discontinue use and consult with your veterinarian.

WARNING:

Keep out of reach of children.

STORAGE CONDITIONS:

Store at room temperature. Do not freeze.

QUESTIONS?

info@aspenveterinaryresources.com

FOR DOGS & CATS

ANTIBACTERIAL ANTIFUNGAL

Manufactured for:
Aspen Veterinary Resources®, LTD. Liberty, MO 64068

pivetalvet.com